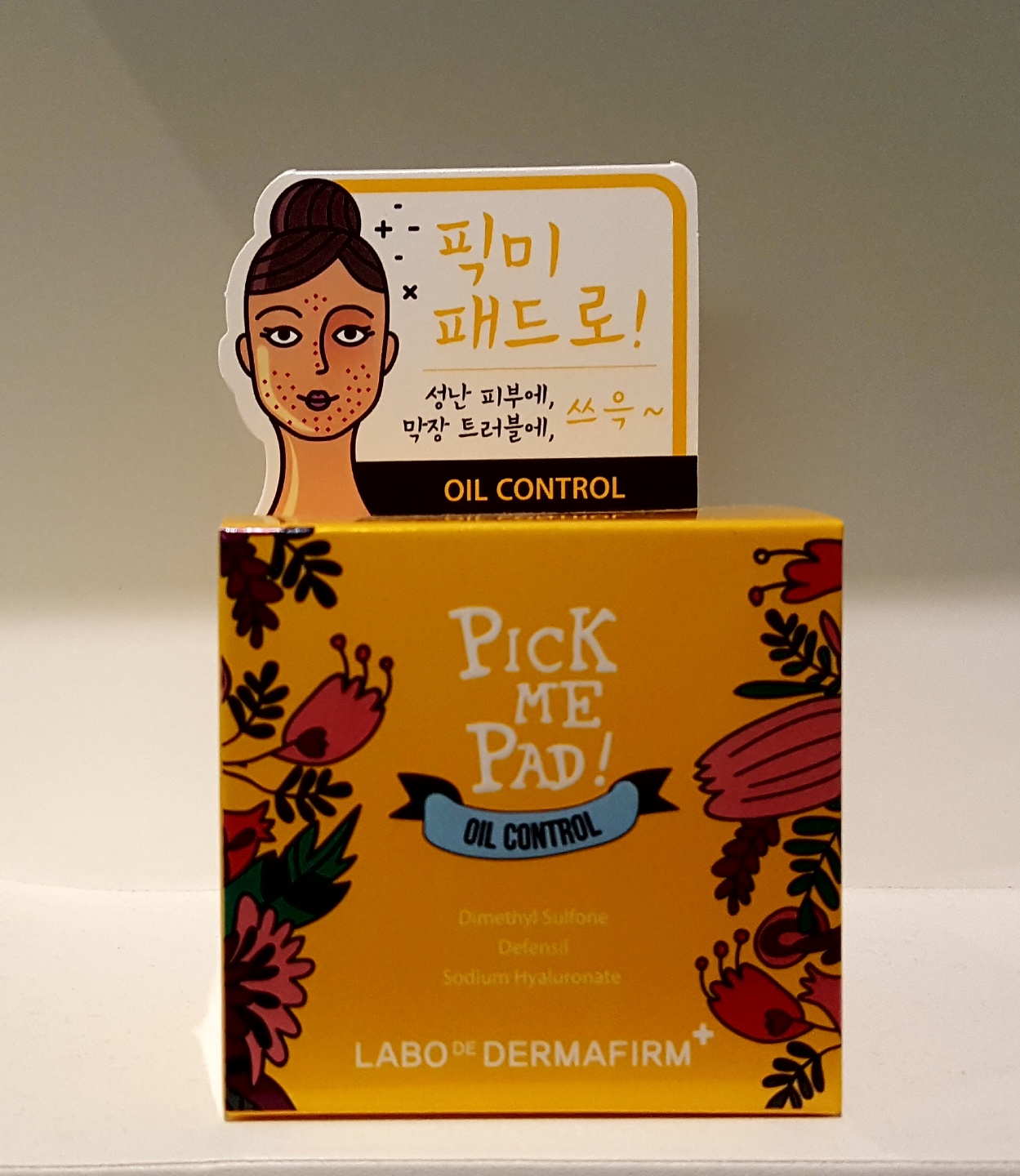 DRUG LABEL: Pick Me Pad Oil Control
NDC: 71638-0007 | Form: LIQUID
Manufacturer: Dermafirm INC.
Category: otc | Type: HUMAN OTC DRUG LABEL
Date: 20170904

ACTIVE INGREDIENTS: GLYCERIN 3.005 g/100 g
INACTIVE INGREDIENTS: WATER; BUTYLENE GLYCOL

Drug Facts

ACTIVE INGREDIENT

Glycerin

INACTIVE INGREDIENT

Water, Butylene Glycol

PURPOSE

Skin protectant

Oil control

keep out of reach of the children

INDICATIONS AND USAGE

After cleansing, gently wipe the entire face with the soft side of the pattern, and gently wipe in the direction of skin texture.

It is better to patch it like a facial pack on the troubled area.

WARNINGS

1. Do not use in the following cases(Eczema and scalp wounds)
2.Side Effects
1)Due to the use of this druf if rash, irritation, itching and symptopms of hypersnesitivity occur dicontinue use and consult your phamacisr or doctor
3.General Precautions
1)If in contact with the eyes, wash out thoroughty with water If the symptoms are servere, seek medical advice immediately
2)This product is for exeternal use only. Do not use for internal use
4.Storage and handling precautions
1)If possible, avoid direct sunlight and store in cool and area of low humidity
2)In order to maintain the quality of the product and avoid misuse
3)Avoid placing the product near fire and store out in reach of children

DOSAGE AND ADMINISTRATION

for external use only